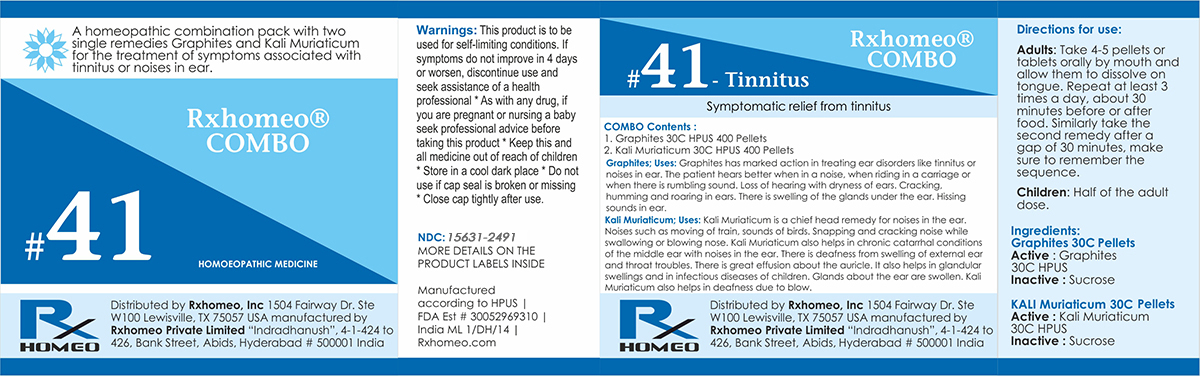 DRUG LABEL: Rxhomeo Homeopathic Combo-41
NDC: 15631-2491 | Form: KIT | Route: ORAL
Manufacturer: Rxhomeo Private Limited d.b.a.
Category: homeopathic | Type: HUMAN OTC DRUG LABEL
Date: 20161016

ACTIVE INGREDIENTS: GRAPHITE 1 [hp_X]/1 1; POTASSIUM CHLORIDE 1 [hp_X]/1 1
INACTIVE INGREDIENTS: SUCROSE; SUCROSE

ACTIVE INGREDIENT

GRAPHITES HPUS 1X and higher

KALI MURIATICUM HPUS 1X and higher

USES

A homeopathic combination pack with two single remedies Graphites and Kali Muriaticum for the treatment of symptoms associated with tinnitus or noises in ear.

Graphites;Uses: Graphites has marked action in treating ear disorders like tinnitus or noises in ear. The patient hears better when in a noise, when riding in a carriage or when there is rumbling sound. Loss of hearing with dryness of ears. Cracking, humming and roaring in ears. There is swelling of the glands under the ear. Hissing sounds in ear.

Kali Muriaticum;Uses: Kali Muriaticum is a chief head remedy for noises in the ear. Noises such as moving of train, sounds of birds. Snapping and cracking noise while swallowing or blowing nose. Kali Muriaticum also helps in chronic catarrhal conditions of the middle ear with noises in the ear. There is deafness from swelling of external ear and throat troubles. There is great effusion about the auricle. It also helps in glandular swellings and in infectious diseases of children. Glands about the ear are swollen. Kali Muriaticum also helps in deafness due to blow.

INDICATIONS

Condition listed above or as directed by the physician

DOSAGE

PELLETS included in the Combo

Adults- Take 4 or 6 Pellets by mouth, three times daily or as suggested by physician. Children 2 years and older- take 1/2 the adult dose.

WARNINGS

This product is to be used for self-limiting conditions

STOP USE

If symptoms do not improve in 4 days, or worsen, discontinue use and seek assistance of health professional

KEEP OUT OF REACH OF CHILDREN

Keep this and all medication out of reach of children

Do not use if capseal is broken or missing.

Close the cap tightly after use.

INACTIVE INGREDIENTS

Sucrose for Pellets.

STORAGE

Store in a cool dark place

QUESTIONS OR COMMENTS

www.Rxhomeo.com | 1.888.2796642 | info@rxhomeo.com
Rxhomeo, Inc 1504 Fairway Dr. Ste W 100 Lewisville, TX 75057 USA